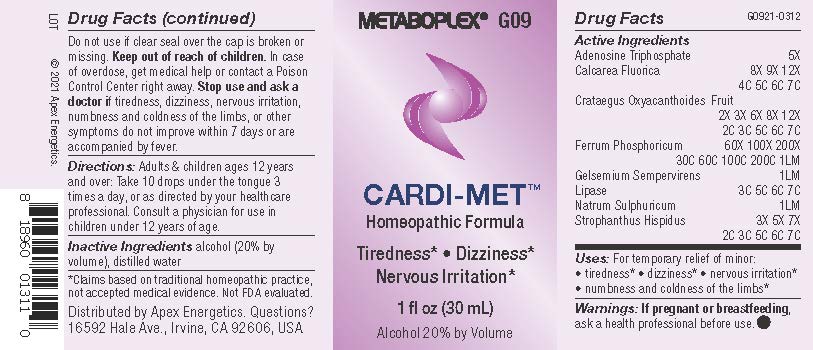 DRUG LABEL: G09
NDC: 63479-0709 | Form: SOLUTION/ DROPS
Manufacturer: Apex Energetics Inc.
Category: homeopathic | Type: HUMAN OTC DRUG LABEL
Date: 20240108

ACTIVE INGREDIENTS: ADENOSINE TRIPHOSPHATE 5 [hp_X]/1 mL; CALCIUM FLUORIDE 7 [hp_C]/1 mL; SODIUM SULFATE 1 [hp_Q]/1 mL; STROPHANTHUS HISPIDUS SEED 7 [hp_C]/1 mL; CRATAEGUS LAEVIGATA FRUIT 7 [hp_C]/1 mL; FERROSOFERRIC PHOSPHATE 1 [hp_Q]/1 mL; GELSEMIUM SEMPERVIRENS ROOT 1 [hp_Q]/1 mL; PANCRELIPASE LIPASE 7 [hp_C]/1 mL
INACTIVE INGREDIENTS: ALCOHOL; WATER

G09

Active Ingredients
Adenosine Triphosphate | 5X
Calcarea Fluorica | 8X 9X 12X 4C 5C 6C 7C
Crataegus Oxyacanthoides Fruit | 2X 3X 6X 8X 12X 2C 3C 5C 6C 7C
Ferrum Phosphoricum | 60X 100X 200X 30C 60C 100C 200C 1LM
Gelsemium Sempervirens | 1LM
Lipase | 3C 5C 6C 7C
Natrum Sulphuricum | 1LM
Strophanthus Hispidus | 3X 5X 7X 2C 3C 5C 6C 7C

INDICATIONS AND USAGE

Uses:

For temporary relief of minor:

tiredness*

dizziness*

nervous irritation*

numbness and coldness of the limbs*

*Claims based on traditional homeopathic practice, not accepted medical evidence. Not FDA evaluated.

Warnings:

PREGNANCY OR BREAST FEEDING

If pregnant or breastfeeding, ask a health professional before use.

Do not use if clear seal over the cap is broken or missing.

Keep out of reach of children. In case of overdose, get medical help or contact a Poison Control Center right away.

Stop use and ask a doctor if tiredness, dizziness, nervous irritation, numbness and coldness of the limbs, or other symptoms do not improve within 7 days or are accompanied by fever.

Directions:

Adults & children ages 12 years and over: Take 10 drops under the tongue 3 times a day, or as directed by your healthcare professional. Consult a physician for use in children under 12 years of age.

Inactive Ingredients

alcohol (20% by volume), distilled water

Distributed by Apex Energetics. Questions?

16592 Hale Ave., Irvine, CA 92606, USA

PACKAGE LABEL

METABOPLEX® G09

CARDI-MET™

Homeopathic Formula

Tiredness*

Dizziness*

Nervous Irritation*

1 fl oz (30 mL)

Alcohol 20% by Volume